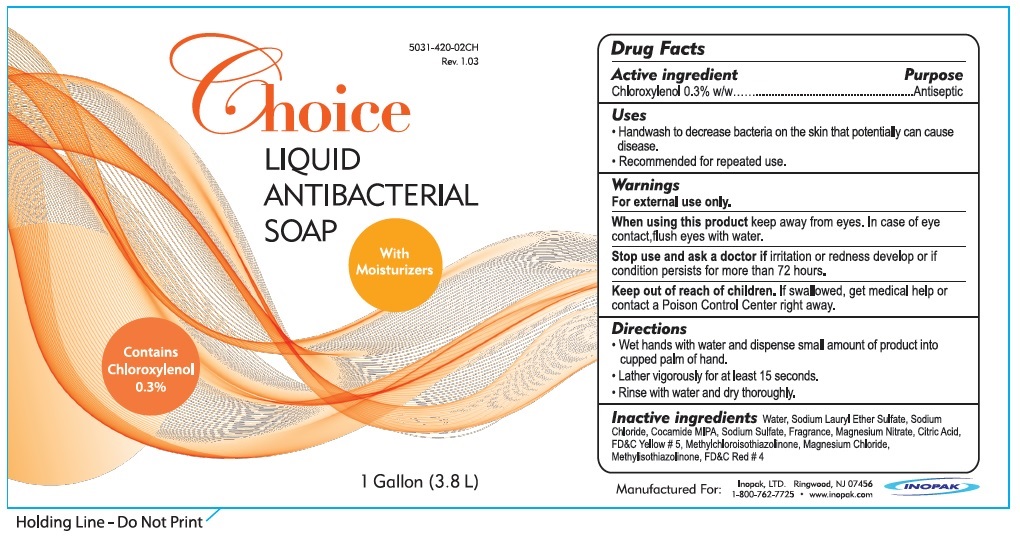 DRUG LABEL: Inoderm Choice Antibacterial
NDC: 73062-523 | Form: LIQUID
Manufacturer: Avro Enterprises LLC
Category: otc | Type: HUMAN OTC DRUG LABEL
Date: 20231028

ACTIVE INGREDIENTS: CHLOROXYLENOL 3 mg/1 mL
INACTIVE INGREDIENTS: WATER; SODIUM LAURETH-3 SULFATE; SODIUM CHLORIDE; COCO MONOISOPROPANOLAMIDE; SODIUM SULFATE; MAGNESIUM NITRATE; CITRIC ACID MONOHYDRATE; FD&C YELLOW NO. 5; METHYLCHLOROISOTHIAZOLINONE; MAGNESIUM CHLORIDE; METHYLISOTHIAZOLINONE; FD&C RED NO. 4

Inoderm Choice Antibacterial Soap

Active ingredient

Chloroxylenol 0.3% w/w

Purpose

Antiseptic

Uses

- Handwash to decrease bacteria on the skin that potentially can cause disease.
- Recommended for repeated use.

Warnings

For external use only

When using this product

keep away from eyes. In case of eye contact, flush eyes with water.

Stop use and ask a doctor if

irritation or redness develop or if condition persists for more than 72 hours.

Keep out of reach of children.

If swallowed, get medical help or contact a Poison Control Center right away.

Directions

- Wet hands with water and dispense small amount of product into cupped palm of hand.
- Lather vigorously for at least 15 seconds.
- Rinse with water and dry thoroughly.

Inactive ingredients

Water, Sodium Lauryl Ether Sulfate, Sodium Chloride, Cocamide MIPA, Sodium Sulfate, Fragrance, Magnesium Nitrate, Citric Acid, FD&C Yellow # 5, Methylchloroisothiazolinone, Magnesium Chloride, Methylsothiazolinone, FD&C Red # 4